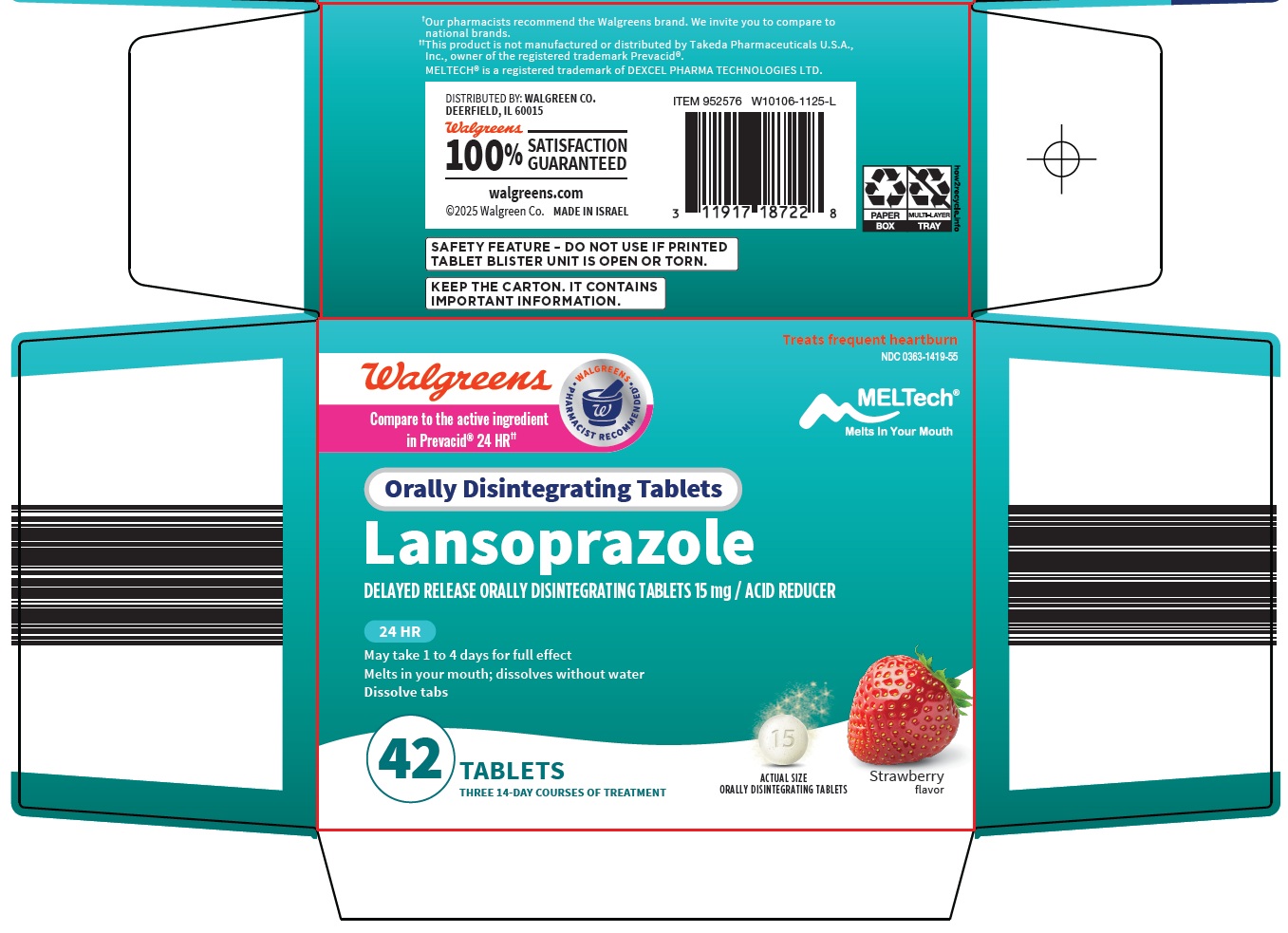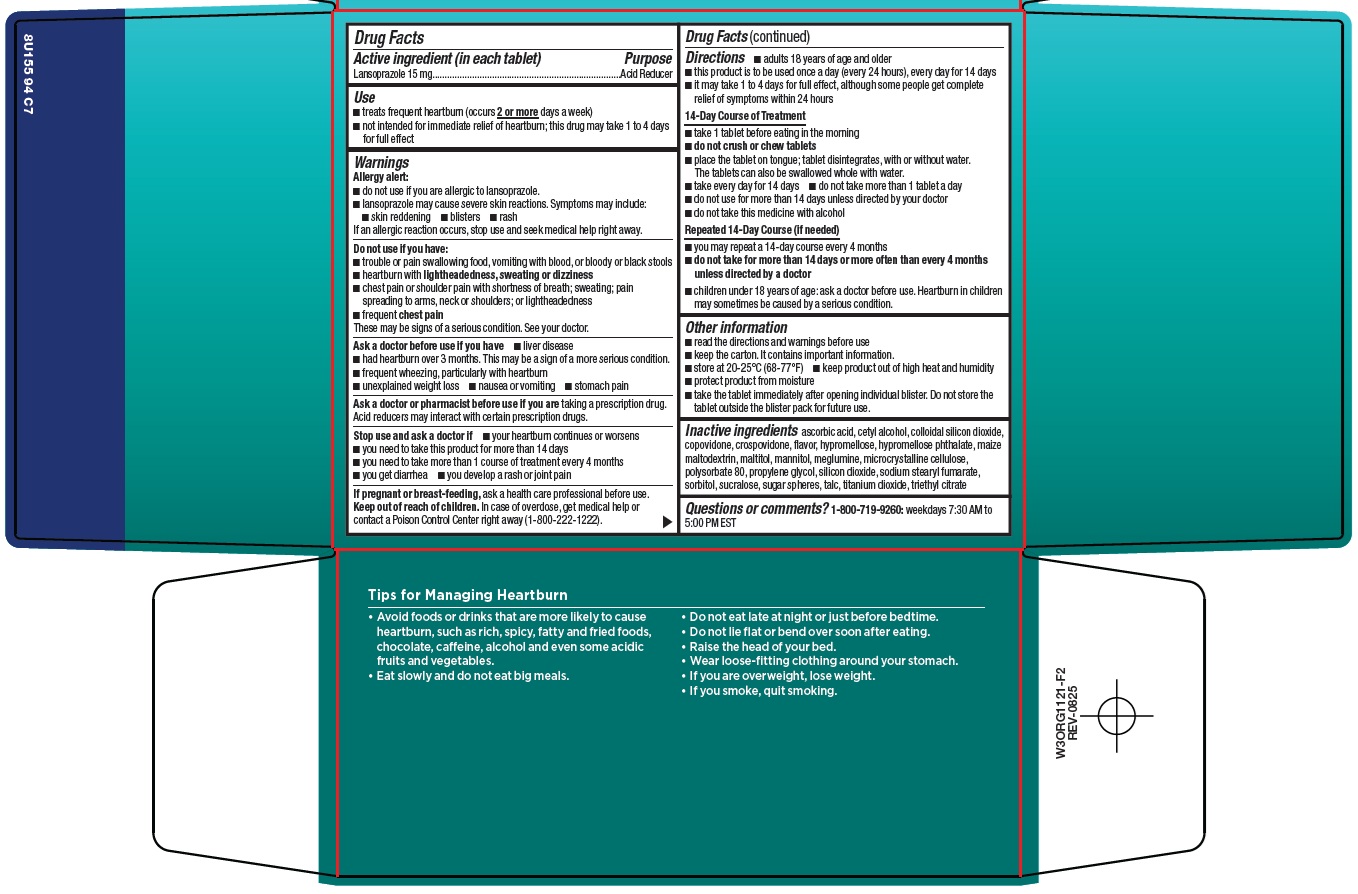 DRUG LABEL: Lansoprazole
NDC: 0363-1419 | Form: TABLET, ORALLY DISINTEGRATING, DELAYED RELEASE
Manufacturer: Walgreen Company
Category: otc | Type: HUMAN OTC DRUG LABEL
Date: 20260228

ACTIVE INGREDIENTS: LANSOPRAZOLE 15 mg/1 1
INACTIVE INGREDIENTS: ASCORBIC ACID; CETYL ALCOHOL; SILICON DIOXIDE; COPOVIDONE K25-31; CROSPOVIDONE, UNSPECIFIED; HYPROMELLOSE, UNSPECIFIED; MALTITOL; MANNITOL; MEGLUMINE; MICROCRYSTALLINE CELLULOSE; POLYSORBATE 80; PROPYLENE GLYCOL; SODIUM STEARYL FUMARATE; SORBITOL; SUCRALOSE; TALC; TITANIUM DIOXIDE; TRIETHYL CITRATE

Walgreen Co. Lansoprazole Drug Facts

Active ingredient (in each tablet)

Lansoprazole 15 mg

Purpose

Acid Reducer

Use

- treats frequent heartburn (occurs 2 or more days a week)
- not intended for immediate relief of heartburn; this drug may take 1 to 4 days for full effect

Warnings

Allergy alert:

• do not use if you are allergic to lansoprazole.

• lansoprazole may cause severe skin reactions. Symptoms may include:

• skin reddening
• blisters
• rash

If an allergic reaction occurs, stop use and seek medical help right away.

Do not use if you have:

- trouble or pain swallowing food, vomiting with blood, or bloody or black stools
- heartburn with lightheadedness, sweating or dizziness
- chest pain or shoulder pain with shortness of breath; sweating; pain spreading to arms; neck or shoulders; or lightheadedness
- frequent chest pain

These may be signs of a serious condition. See your doctor.

Ask a doctor before use if you have

- liver disease
- had heartburn over 3 months. This may be a sign of a more serious condition.
- frequent wheezing, particularly with heartburn
- unexplained weight loss
- nausea or vomiting
- stomach pain

Ask a doctor or pharmacist before use if you are

taking a prescription drug. Acid reducers may interact with certain prescription drugs.

Stop use and ask a doctor if

- your heartburn continues or worsens
- you need to take this product for more than 14 days
- you need to take more than 1 course of treatment every 4 months
- you get diarrhea
- you develop a rash or joint pain

If pregnant or breast-feeding,

ask a health care professional before use.

Keep out of reach of children.

In case of overdose, get medical help or contact a Poison Control Center right away (1-800-222-1222).

Directions

- adults 18 years of age and older
- this product is to be used once a day (every 24 hours), every day for 14 days
- it may take 1 to 4 days for full effect, although some people get complete relief of symptoms within 24 hours

14-Day Course of Treatment

- take 1 tablet before eating in the morning
- do not crush or chew tablets
- place the tablet on tongue; tablet disintegrates, with or without water. The tablets can also be swallowed whole with water.
- take every day for 14 days
- do not take more than 1 tablet a day
- do not use for more than 14 days unless directed by your doctor
- do not take this medicine with alcohol

Repeated 14-Day Course (if needed)

- you may repeat a 14-day course every 4 months
- do not take for more than 14 days or more often than every 4 months unless directed by a doctor
- children under 18 years of age: ask a doctor before use. Heartburn in children may sometimes be caused by a serious condition.

Other information

- read the directions and warnings before use
- keep the carton. It contains important information.
- store at 20-25°C (68-77°F)
- keep product out of high heat and humidity
- protect product from moisture
- take the tablet immediately after opening individual blister. Do not store the tablet outside the blister pack for future use.

Inactive ingredients

ascorbic acid, cetyl alcohol, colloidal silicon dioxide, copovidone, crospovidone, flavor, hypromellose, hypromellose phthalate, maize maltodextrin, maltitol, mannitol, meglumine, microcrystalline cellulose, polysorbate 80, propylene glycol, silicon dioxide, sodium stearyl fumarate, sorbitol, sucralose, sugar spheres, talc, titanium dioxide, triethyl citrate

Questions or comments?

1-800-719-9260: weekdays 7:30 AM to 5:00 PM EST

Package/Label Principal Display Panel

Treats frequent heartburn

Walgreens

WALGREENS PHARMACIST RECOMMENDED

MELTech®

Melts In Your Mouth

Compare to the active ingredient in Prevacid® 24 HR

Orally Disintegrating Tablets

Lansoprazole

DELAYED RELEASE ORALLY DISINTEGRATING TABLETS 15 mg / ACID REDUCER

24 HR

May take 1 to 4 days for full effect

Melts in your mouth; dissolves without water

Dissolve tabs

42 TABLETS

THREE 14-DAY COURSES OF TREATMENT

ACTUAL SIZE

ORALLY DISINTEGRATING TABLETS

Strawberry flavor